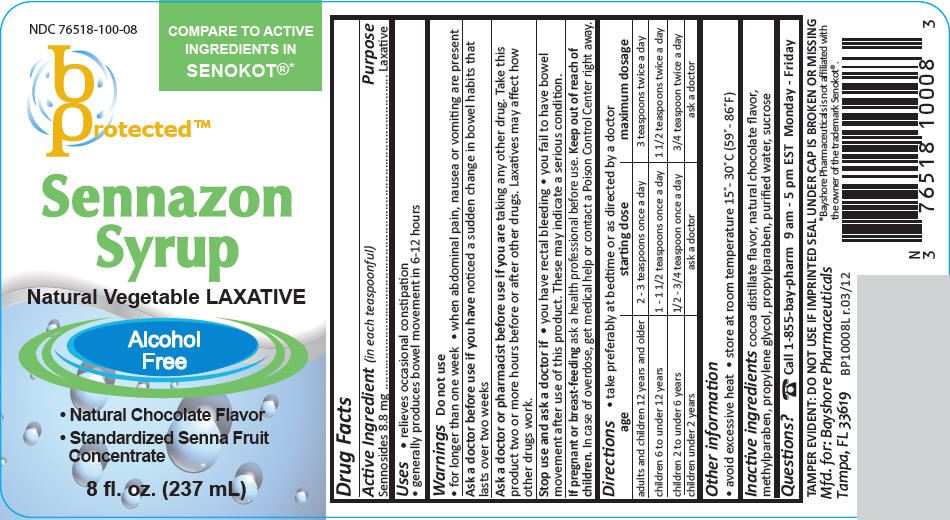 DRUG LABEL: Sennazon
NDC: 76518-100 | Form: SYRUP
Manufacturer: Bayshore Pharmaceuticals LLC [FL]
Category: otc | Type: HUMAN OTC DRUG LABEL
Date: 20130731

ACTIVE INGREDIENTS: Sennosides A and B 8.8 mg/5 mL
INACTIVE INGREDIENTS: Methylparaben; propylene glycol; propylparaben; water; sucrose; cocoa

Sennazon Syrup

Drug Facts

Active Ingredient (in each teaspoonful)

Sennosides 8.8 mg

Purpose

Laxative

Uses

- relieves occasional constipation
- generally produces bowel movement in 6-12 hours

Warnings

Do not use

- for longer than one week
- when abdominal pain, nausea or vomiting are present

Ask a doctor before use if you have noticed a sudden change in bowel habits that lasts over two weeks

Ask a doctor or pharmacist before use if you are taking any other drug. Take this product two or more hours before or after other drugs. Laxatives may affect how other drugs work.

Stop use and ask a doctor if

- you have rectal bleeding
- you fail to have bowel movement after use of this product. These may indicate a serious condition.

PREGNANCY OR BREAST FEEDING

If pregnant or breast-feeding ask a health professional before use.

Keep out of reach of children. In case of overdose, get medical help or contact a Poison Control Center right away.

Directions

- take preferably at bedtime or as directed by a doctor

age | starting dose | maximum dosage
adults and children 12 years and older | 2 - 3 teaspoons once a day | 3 teaspoons twice a day
children 6 to under 12 years | 1 - 1 1/2 teaspoons once a day | 1 1/2 teaspoons twice a day
children 2 to under 6 years | 1/2 - 3/4 teaspoon once a day | 3/4 teaspoon twice a day
children under 2 years | ask a doctor | ask a doctor

Other information

- avoid excessive heat
- store at room temperature 15°- 30°C (59°- 86°F)

Inactive ingredients

cocoa distillate flavor, natural chocolate flavor, methylparaben, propylene glycol, propylparaben, purified water, sucrose

Questions?

Call 1-855-bay-pharm 9 am - 5 pm EST Monday - Friday

Mfd. for: Bayshore Pharmaceuticals
Tampa, FL 33619

PRINCIPAL DISPLAY PANEL - 237 mL Bottle Label

NDC 76518-100-08

COMPARE TO ACTIVE
INGREDIENTS IN
SENOKOT®*

b
Protected™

Sennazon
Syrup

Natural Vegetable LAXATIVE

Alcohol
Free

- Natural Chocolate Flavor
- Standardized Senna Fruit
  Concentrate

8 fl. oz. (237 mL)